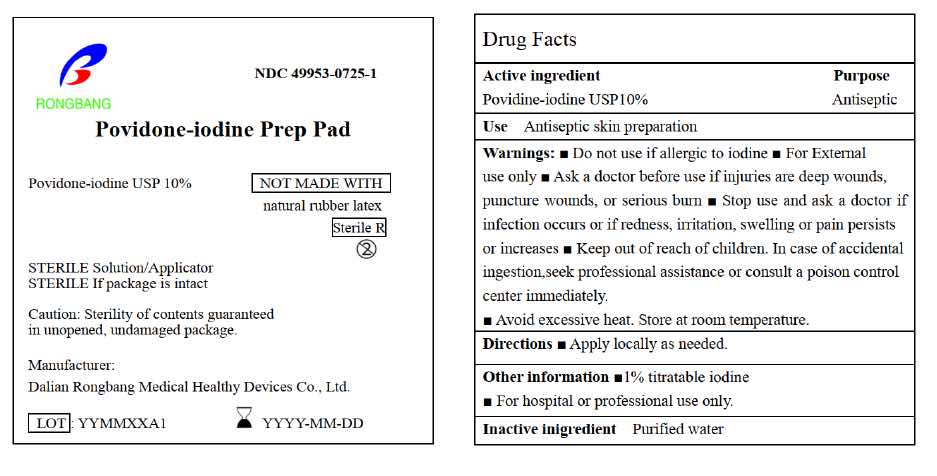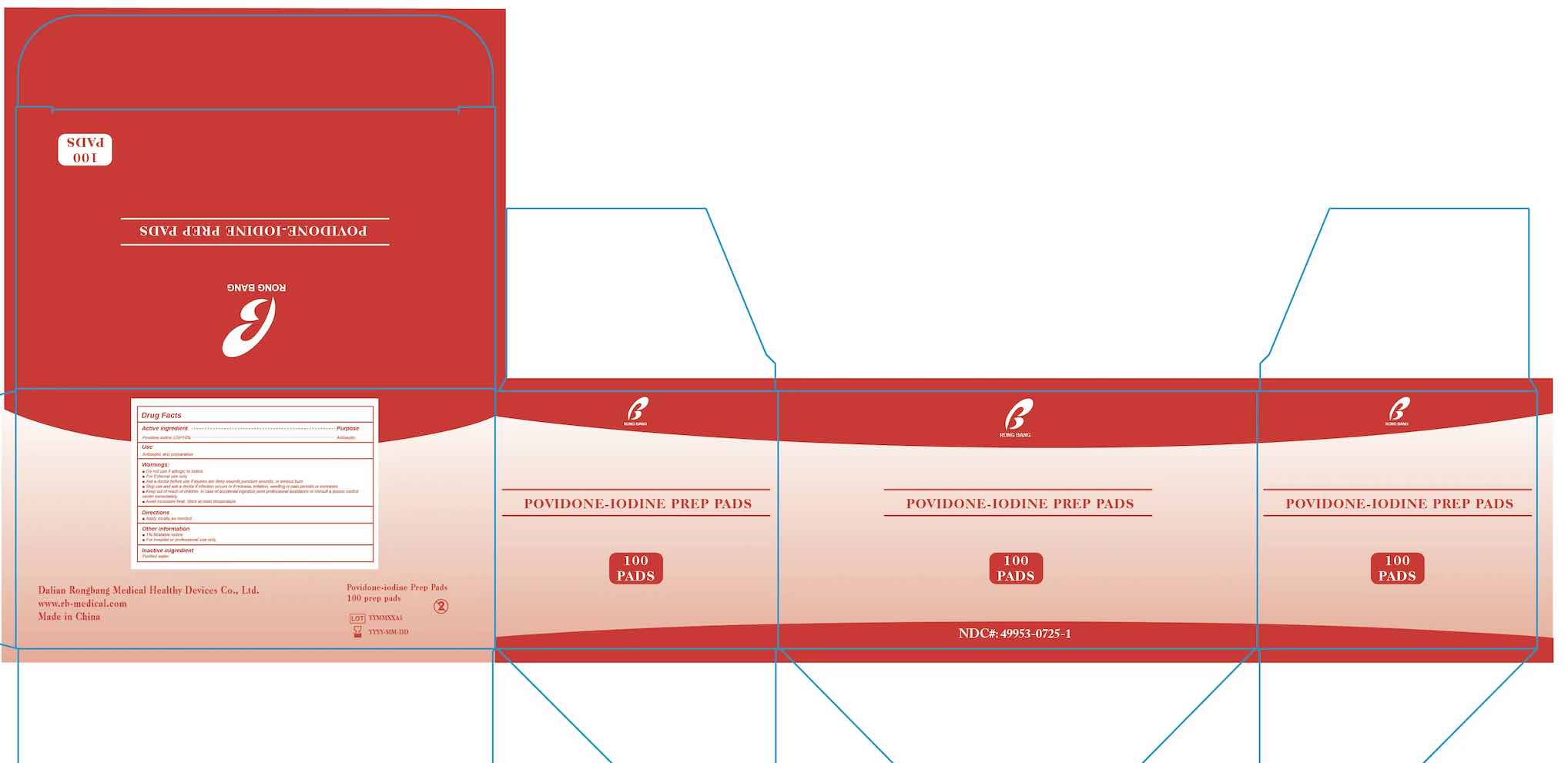 DRUG LABEL: Povidon Iodine Prep Pads
NDC: 49953-0725 | Form: SWAB
Manufacturer: Dalian Rongbang Medical Healthy Devices Co., Ltd.
Category: otc | Type: HUMAN OTC DRUG LABEL
Date: 20231228

ACTIVE INGREDIENTS: POVIDONE-IODINE 10 mg/1 mL
INACTIVE INGREDIENTS: WATER

Dalian Rongbang Povidone-Iodine Prep Pads

ACTIVE INGREDIENT

Povidone-Iodine USP 10%

PURPOSE

Antiseptic

USE

Antiseptic Skin Preparation

WARNINGS

For External use only

Avoid excessive heat. Store at room temperature.

Do not use if allergic to iodine

Stop use and ask a doctor if infection occurs or if redness, irriation, swelling or pain persists or increases

Keep out of reach of children. In case of accidentla ingestion, seek professional assistance or consult a poision control center immediately

DIRECTIONS

Apply locally as needed

OTHER INFORMATION

1% titratable iodine

For hospital or professional use only

INACTIVE INGREDIENT

Purified water